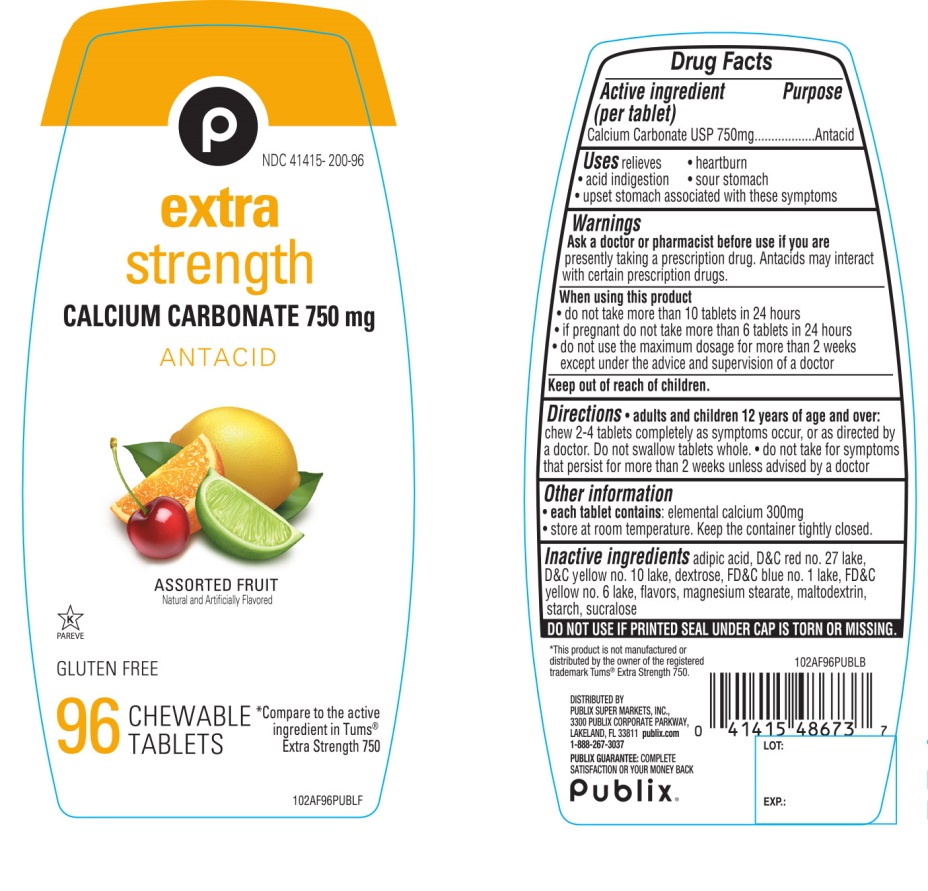 DRUG LABEL: Publix Extra Strength
NDC: 41415-200 | Form: TABLET, CHEWABLE
Manufacturer: PUBLIX SUPER MARKETS, INC
Category: otc | Type: HUMAN OTC DRUG LABEL
Date: 20211109

ACTIVE INGREDIENTS: CALCIUM CARBONATE 750 mg/1 1
INACTIVE INGREDIENTS: ADIPIC ACID; D&C RED NO. 27; D&C YELLOW NO. 10; DEXTROSE, UNSPECIFIED FORM; FD&C BLUE NO. 1; FD&C YELLOW NO. 6; MAGNESIUM STEARATE; MALTODEXTRIN; STARCH, CORN; SUCRALOSE

Publix® Extra Strength Assorted Fruits 96 Chewable Tablets

Active ingredient (per tablet)

Calcium Carbonate USP 750mg

Purpose

Antacid

Uses

relieves

- heartburn
- sour stomach
- acid indigestion
- upset stomach associated with these symptoms

Warnings

Ask a doctor or pharmacist before use if you are presentlytaking a prescription drug. Antacids may interact with certain prescription drugs.

When using this product

- do not take more than 10 tablets in 24 hours
- if pregnant do not take more than 6 tablets in 24 hours
- do not use the maximum dosage for more than 2 weeks except under the advice and supervision of a doctor.

Directions

- adults and children 12 years of age and over: chew 2-4 tablets completely as symptoms occur, or as directed by a doctor. Do not swallow tablets whole.
- do not take for symptoms that persist for more than 2 weeks unless advised by a doctor.

Other information

- each tablet contains: elemental calcium 300mg
- store at room temperature. Keep the container tightly closed

SAFETY SEALED: Do not use if printed seal under cap is torn or missing

Inactive ingredients

adipic acid, D&C red # 27 lake, D&C yellow # 10 lake, dextrose, FD&C blue # 1 lake, FD&C yellow # 6 lake, flavors, magnesium stearate, maltodextrin, starch, sucralose,

Questions or comments?

1-888-267-3037

Package/Label Principal Display Panel

Publix®

NDC# 41415-200-96

Compare to the active ingredients in Tums® Extra Strength 750 Assorted Fruit Flavor

extra strength

CALCIUM CARBONATE 750 mg/ ANTACID

ASSORTED FRUIT

Natural and Artificially Flavored

96 CHEWABLE TABLETS

GLUTEN-FREE

DISTRIBUTED BY:

PUBLIX SUER MARKETS, INC.,

LAKELAND, FL 33811 publix.com

1-888-267-3037

PUBLIX GUARANTEE: COMPLETE SATISFACTION OR YOUR MONEY BACK

*This product is not manufactured or distributed by GlaxoSmithKline, owner of the registered trademark Tums® Extra Strength